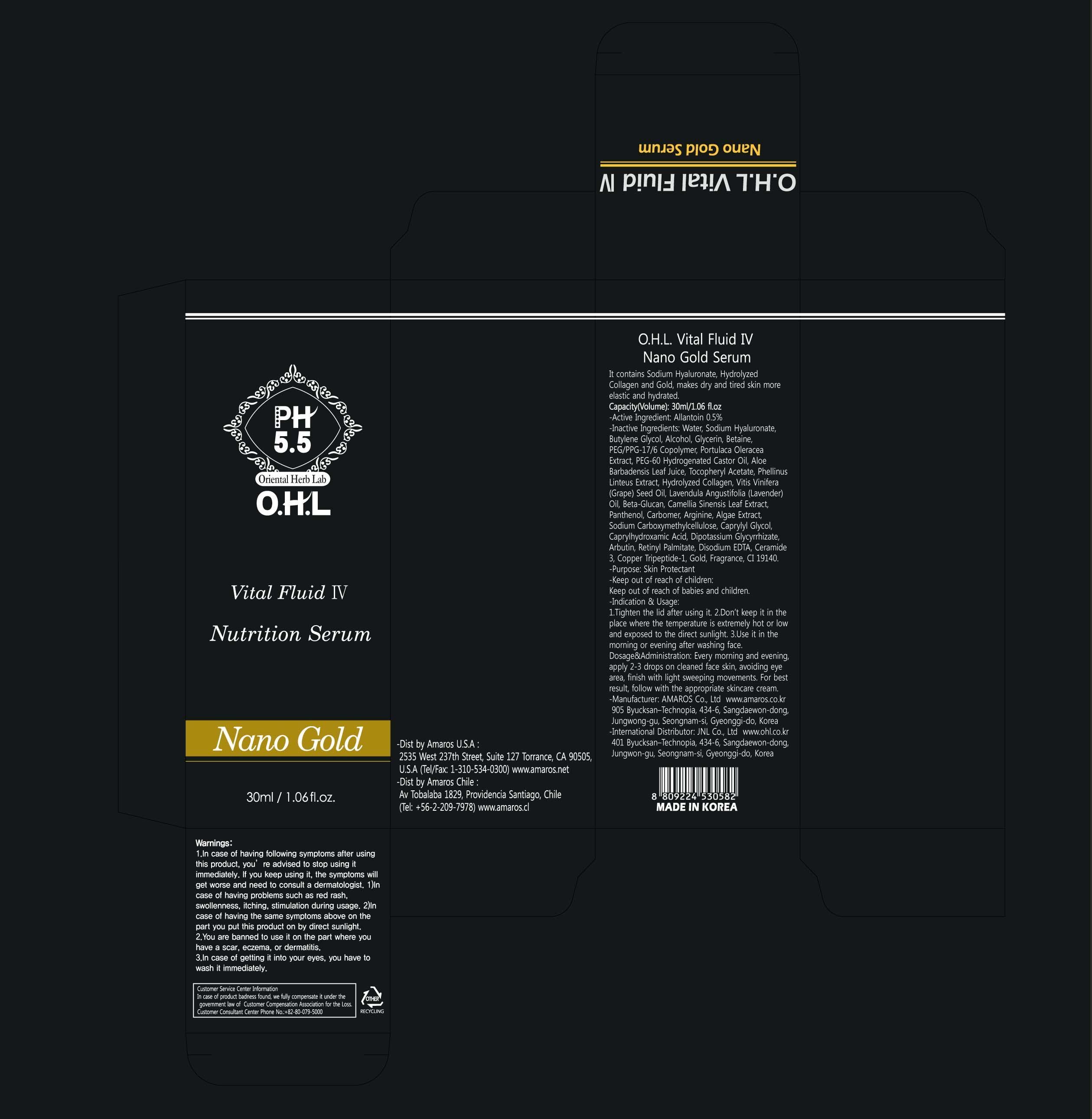 DRUG LABEL: Vital Fluid IV Nano Gold Serum
NDC: 60899-090 | Form: CREAM
Manufacturer: AMAROS CO., LTD.
Category: otc | Type: HUMAN OTC DRUG LABEL
Date: 20190411

ACTIVE INGREDIENTS: Allantoin 0.15 mg/30 mL
INACTIVE INGREDIENTS: Water; Alcohol

ACTIVE INGREDIENT

Active Ingredient: Allantoin 0.5%

INACTIVE INGREDIENT

Inactive Ingredients: Water, Sodium Hyaluronate, Butylene Glycol, Alcohol, Glycerin, Betaine, PEG/PPG-17/6 Copolymer, Portulaca Oleracea Extract, PEG-60 Hydrogenated Castor Oil, Aloe Barbadensis Leaf Juice, Tocopheryl Acetate, Phellinus Linteus Extract, Hydrolyzed Collagen, Vitis Vinifera (Grape) Seed Oil, Lavendula Angustifolia (Lavender) Oil, Beta-Glucan, Camellia Sinensis Leaf Extract, Panthenol, Carbomer, Arginine, Algae Extract, Sodium Carboxymethylcellulose, Caprylyl Glycol, Caprylhydroxamic Acid, Dipotassium Glycyrrhizate, Arbutin, Retinyl Palmitate, Disodium EDTA, Ceramide 3, Copper Tripeptide-1, Gold, Fragrance, CI 19140.

PURPOSE

Purpose: Skin Protectant

WARNINGS

Warnings: 1. In case of having following symptoms after using this product, you're advised to stop using it immediately. If you keep using it, the symptoms will get worse and need to consult a dermatologist. 1) In case of having problems such as red rash, swollenness, itching, stimulation during usage. 2) In case of having the same symptoms above on the part you put this product on by direct sunlight. 2. You are banned to use it on the part where you have a scar, eczema, or dermatitis. 3. In case of getting it into your eyes, you have to wash it immediately.

Keep out of reach of children: Keep out of reach of babies and children.

INDICATIONS AND USAGE

Indication and Usage: 1. Tighten the lid after using it. 2. Don't keep it in the place where the temperature is extremely hot or low and exposed to the direct sunlight.3. Use it in the morning or evening after washing face.

Dosage and Administration: Every morning and evening, apply 2-3 drops on cleaned face skin, avoiding eye area, finish with light sweeping movements. For best result, follow with the appropriate skincare cream.